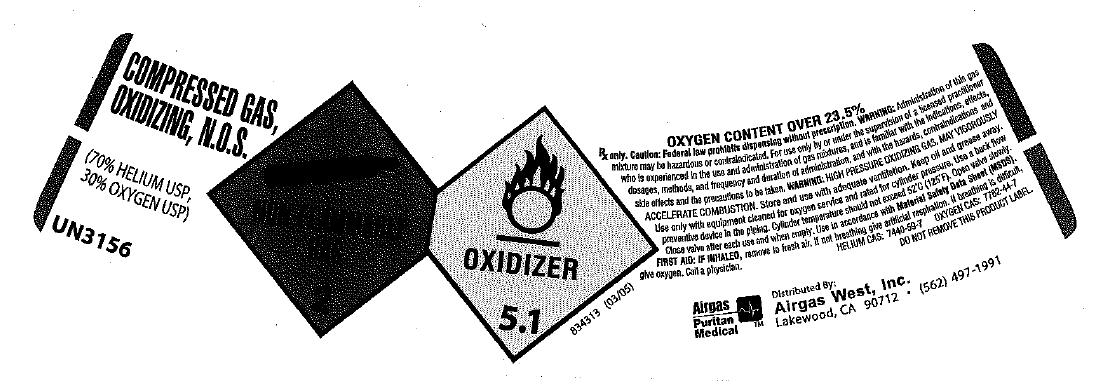 DRUG LABEL: Helium Oxygen Mix 70/30
NDC: 10678-010 | Form: GAS
Manufacturer: Airgas-West, Inc.
Category: prescription | Type: HUMAN PRESCRIPTION DRUG LABEL
Date: 20100527

ACTIVE INGREDIENTS: Helium 700 mL/1 L; Oxygen 300 mL/1 L

He O2 mix 70/30

PACKAGE LABEL

COMPRESSED GAS, N.O.S.
(70% HELIUM USP, 30% OXYGEN USP)
UN3156
NON-FLAMMABLE 2 OXIDIZER 5.1
834313 (03/05)
OXYGEN CONTENT OVER 23.5%
Rx only.CAUTION: Federal law prohibits dispensing without a prescription. WARNING: Administration of this gas mixture may be hazardous or contraindicated. For use by or under the supervision of a licensed practitioner who is experienced in the use and administration of gas mixtures, and is familiar with the indications, effects, dosages, methods, and frequency and duration of administration, and with the hazards, contraindications and side effects, and the precautions to be taken.
CAUTION: HIGH PRESSURE OXIDIZING GAS. MAY VIGOROUSLY ACCELERATE COMBUSTION. Store and use with adequate ventilation. Keep oil and grease away. Use only with equipment cleaned for oxygen service and rated for cylinder pressure. Use a back flow preventive device in the piping. Cylinder temperature should not exceed 52oC(125oF). Open valve slowly. Close valve after each use and when empty. Use in accordance with the Material Safety Data Sheet (MSDS).
FIRST AID: IF INHALED, remove to fresh air. If not breathing, give artificial respiration. If breathing is difficult, give oxygen. Call a physician. HELIUM CAS: 7440-59-7 OXYGEN CAS: 7782-44-7
DO NOT REMOVE THIS PRODUCT LABEL.
AIRGAS PURITAN MEDICAL Distributed By: Airgas West, Inc. Lakewood, CA 90712 (562) 497-1991